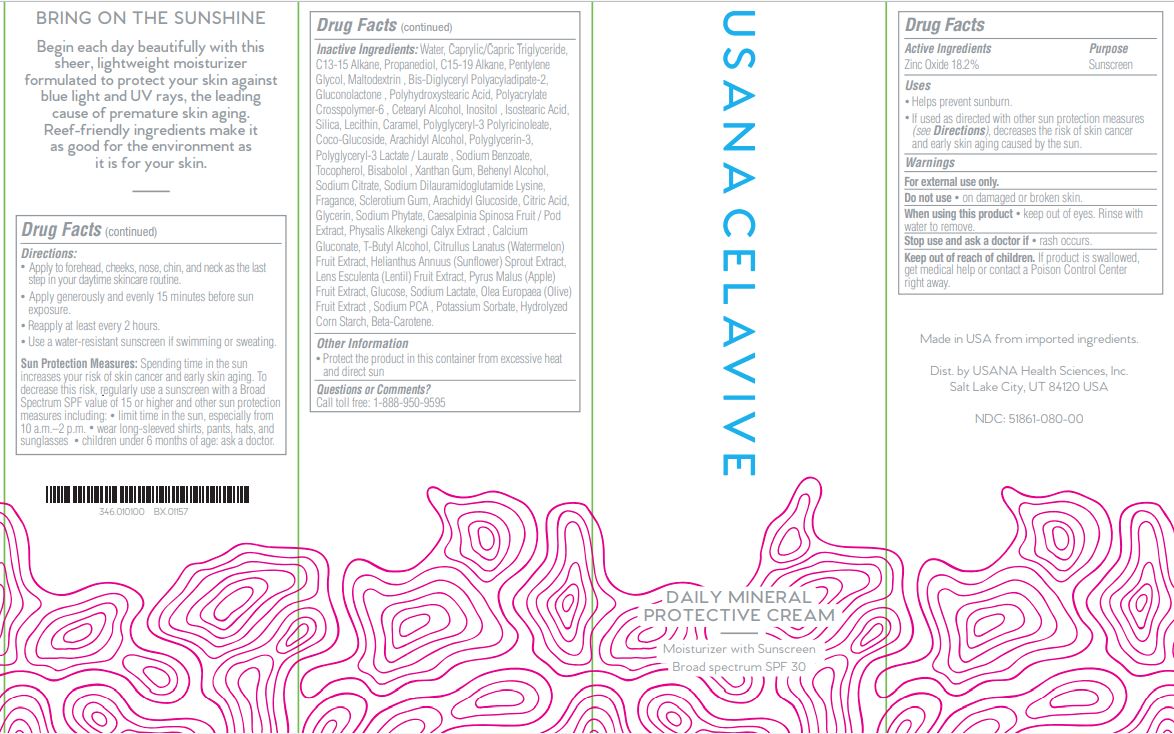 DRUG LABEL: Usana Celavive Daily Mineral Protective Cream Moisturizer with Sunscreen SPF 30
NDC: 51861-080 | Form: CREAM
Manufacturer: USANA Health Sciences, Inc.
Category: otc | Type: HUMAN OTC DRUG LABEL
Date: 20231019

ACTIVE INGREDIENTS: ZINC OXIDE 182 mg/1 mL
INACTIVE INGREDIENTS: SODIUM DILAURAMIDOGLUTAMIDE LYSINE; LECITHIN, SOYBEAN; WATER; C13-15 ALKANE; PROPANEDIOL; C15-19 ALKANE; MEDIUM-CHAIN TRIGLYCERIDES; PENTYLENE GLYCOL; POLYHYDROXYSTEARIC ACID (2300 MW); ISOSTEARIC ACID; POLYGLYCERYL-3 PENTARICINOLEATE; MALTODEXTRIN; BIS-DIGLYCERYL POLYACYLADIPATE-2; GLUCONOLACTONE; AMMONIUM ACRYLOYLDIMETHYLTAURATE, DIMETHYLACRYLAMIDE, LAURYL METHACRYLATE AND LAURETH-4 METHACRYLATE COPOLYMER, TRIMETHYLOLPROPANE TRIACRYLATE CROSSLINKED (45000 MPA.S); INOSITOL; SILICON DIOXIDE; ARACHIDYL ALCOHOL; POLYGLYCERIN-3; POLYGLYCERYL-3 LAURATE; SODIUM BENZOATE; TOCOPHEROL; LEVOMENOL; CETOSTEARYL ALCOHOL; COCO GLUCOSIDE; ANHYDROUS DEXTROSE; XANTHAN GUM; DOCOSANOL; SODIUM CITRATE; BETASIZOFIRAN; ARACHIDYL GLUCOSIDE; CITRIC ACID MONOHYDRATE; CAESALPINIA SPINOSA RESIN; PHYTATE SODIUM; PHYSALIS ALKEKENGI CALYX; TERT-BUTYL ALCOHOL; CALCIUM GLUCONATE; HELIANTHUS ANNUUS SPROUT; LIMONENE, (+)-; BETA CAROTENE

Usana Celavive Daily Mineral Protective Cream Moisturizer with Sunscreen SPF 30

Active Ingredients

Zinc Oxide 18.2%

Purpose

Sunscreen

Uses

- Helps Prevent Sunburn.
- If used as directed with other sun protection measures , decreases the risk of skin cancer and early skin aging caused by the sun. (see) Directions

Warnings

For External use only.

Do not use

- on damaged or broken skin.

When using this product

- keep out of eyes. Rinse with water to remove.

Stop use and ask a doctor if

- rash occurs.

Keep out of reach of children.

If product is swallowed, get medical help or contact a Poison Control Center right away.

Directions:

- Apply to forehead, cheeks, nose, chin, and neck as the last step in your daytime skincare routine.
- Apply generously and evenly 15 minutes before sun exposure.
- Reapply at least every 2 hours.
- Use a water-resistant sunscreen if swimming or sweating.

- limit time in the sun, especially from 10 a.m.–2 p.m.
- wear long-sleeved shirts, pants, hats, and sunglasses
- children under 6 months of age: ask a doctor.

Spending time in the sun increases your risk of skin cancer and early skin aging. To decrease this risk, regularly use a sunscreen with a Broad Spectrum SPF value of 15 or higher and other sun protection measures including: Sun Protection Measures:

Inactive Ingredients:

Water, C13-15 Alkane, Propanediol, C15-19 Alkane, Caprylic/Capric Triglyceride, Pentylene Glycol, Polyhydroxystearic Acid, Isostearic Acid, Lecithin, Polyglyceryl-3 Polyricinoleate, Maltodextrin, Bis-Diglyceryl Polyacyladipate-2, Gluconolactone, Polyacrylate Crosspolymer-6, Inositol, Silica, Arachidyl Alcohol, Polyglycerin-3, Polyglyceryl-3 Lactate/Laurate, Sodium Benzoate, Tocopherol, Bisabolol, Cetearyl Alcohol, Coco- Glucoside, Glucose, Xanthan Gum, Behenyl Alcohol, Sodium Citrate, Sodium Dilauramidoglutamide Lysine, Sclerotium Gum, Fragrance, Arachidyl Glucoside, Citric Acid, Caesalpinia Spinosa Gum, Sodium Phytate, Physalis Alkekengi Calyx Extract, T-Butyl Alcohol, Calcium Gluconate, Helianthus Annuus Sprout Extract, Limonene, Beta-Carotene.

Other Information

- Protect the product in this container from excessive heat and direct sun

Questions or Comments?

Call toll free 1-888-950-9595